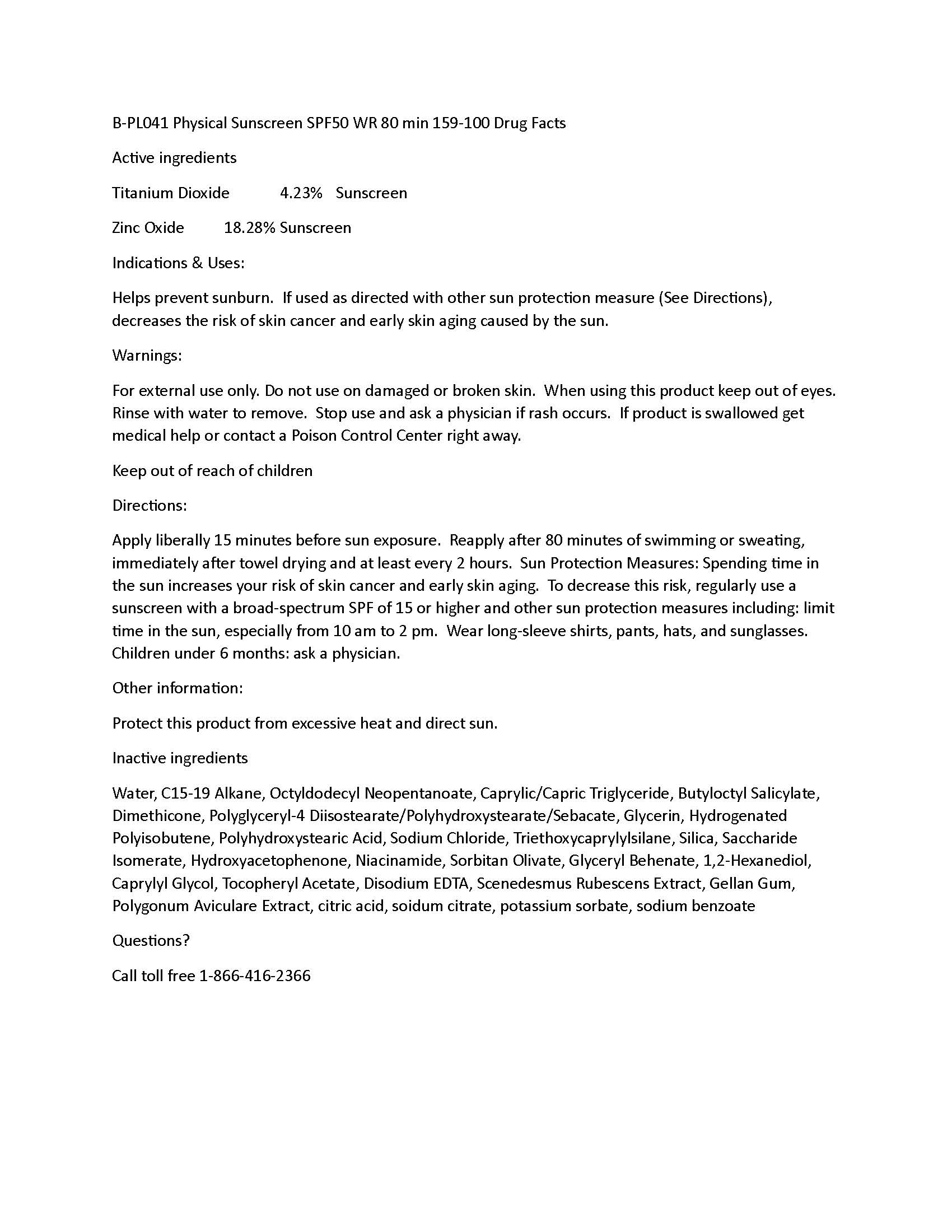 DRUG LABEL: Physical Sunscreen SPF50 80 min WR 159-100
NDC: 60232-0044 | Form: LOTION
Manufacturer: Swiss-American CDMO, LLC
Category: otc | Type: HUMAN OTC DRUG LABEL
Date: 20231109

ACTIVE INGREDIENTS: TITANIUM DIOXIDE 42.3 g/1000 g; ZINC OXIDE 182.8 g/1000 g
INACTIVE INGREDIENTS: WATER; C15-19 ALKANE; OCTYLDODECYL NEOPENTANOATE; BUTYLOCTYL SALICYLATE; DIMETHICONE; POLYGLYCERYL-4 DIISOSTEARATE/POLYHYDROXYSTEARATE/SEBACATE; GLYCERIN; POLYHYDROXYSTEARIC ACID (2300 MW); SODIUM CHLORIDE; TRIETHOXYCAPRYLYLSILANE; SACCHARIDE ISOMERATE; HYDROXYACETOPHENONE; NIACINAMIDE; SORBITAN OLIVATE; 1,2-HEXANEDIOL; CAPRYLYL GLYCOL; EDETATE DISODIUM; PENTYLENE GLYCOL; GELLAN GUM (LOW ACYL); POLYGONUM AVICULARE WHOLE; ANHYDROUS CITRIC ACID; SODIUM CITRATE; POTASSIUM SORBATE; SODIUM BENZOATE; MEDIUM-CHAIN TRIGLYCERIDES; HYDROGENATED POLYBUTENE (1300 MW); SILICON DIOXIDE; GLYCERYL MONOBEHENATE; .ALPHA.-TOCOPHEROL ACETATE

Physical Sunscreen SPF50 80 min WR 159-100

Warnings

For external use only. Do not use on damaged or broken skin. When using this product keep out of eyes. Rinse with water to remove. Stop use and ask a physician if rash occurs. If product is swallowed get medical help or contact a Poison Control Center right away.

Active Ingredients

Titanium Dioxide 4.23% Sunscreen
Zinc Oxide 18.28% Sunscreen

Uses

Helps prevent sunburn. If used as directed with other sun protection measure (See Directions), decreases the risk of skin cancer and early skin aging caused by the sun.

Uses

Helps prevent sunburn. If used as directed with other sun protection measure (See Directions), decreases the risk of skin cancer and early skin aging caused by the sun.

Directions

Apply liberally 15 minutes before sun exposure. Reapply after 80 minutes of swimming or sweating, immediately after towel drying and at least every 2 hours. Sun Protection Measures: Spending time in the sun increases your risk of skin cancer and early skin aging. To decrease this risk, regularly use a sunscreen with a broad-spectrum SPF of 15 or higher and other sun protection measures including: limit time in the sun, especially from 10 am to 2 pm. Wear long-sleeve shirts, pants, hats, and sunglasses. Children under 6 months: ask a physician.

Keep out of reach of children

Inactive ingredients

Water, C15-19 Alkane, Octyldodecyl Neopentanoate, Caprylic/Capric Triglyceride, Butyloctyl Salicylate, Dimethicone, Polyglyceryl-4 Diisostearate/Polyhydroxystearate/Sebacate, Glycerin, Hydrogenated Polyisobutene, Polyhydroxystearic Acid, Sodium Chloride, Triethoxycaprylylsilane, Silica, Saccharide Isomerate, Hydroxyacetophenone, Niacinamide, Sorbitan Olivate, Glyceryl Behenate, 1,2-Hexanediol, Caprylyl Glycol, Tocopheryl Acetate, Disodium EDTA, Scenedesmus Rubescens Extract, Gellan Gum, Polygonum Aviculare Extract, citric acid, sodium citrate, potassium sorbate, sodium benzoate

Other information

Protect this product from excessive heat and direct sun.

Questions

Call toll free 1-866-416-2366